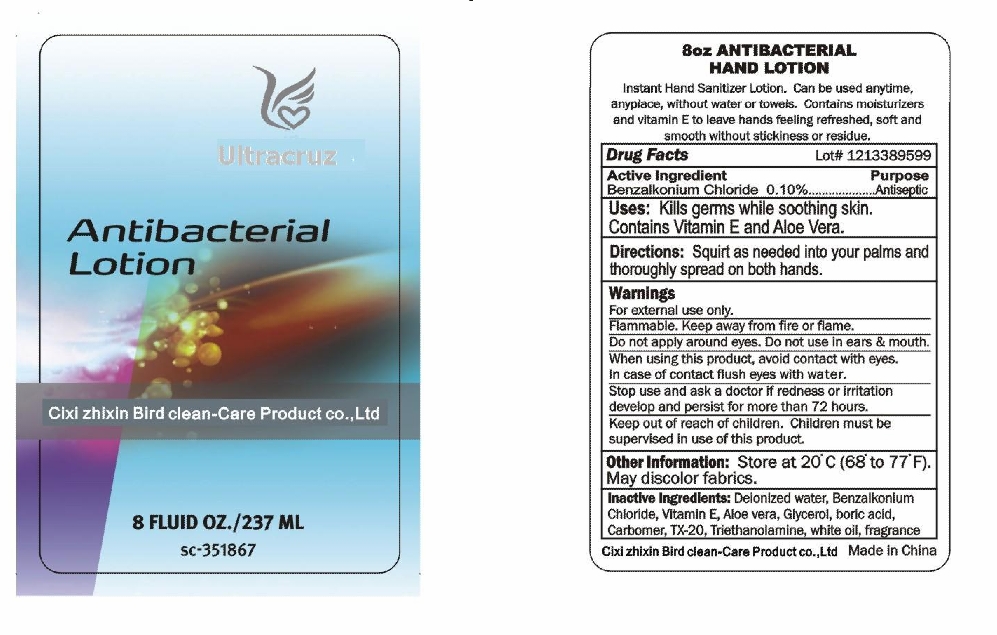 DRUG LABEL: Ultracruz Antibacterial
NDC: 49877-011 | Form: LOTION
Manufacturer: Cixi Zhixin Bird Clean-care Product Co., Ltd.
Category: otc | Type: HUMAN OTC DRUG LABEL
Date: 20140822

ACTIVE INGREDIENTS: BENZALKONIUM CHLORIDE 0.1 g/100 mL
INACTIVE INGREDIENTS: WATER 96.105 g/100 mL; TROLAMINE; ALPHA-TOCOPHEROL; GLYCEROL FORMAL; ALOE; CARBOMER HOMOPOLYMER TYPE C; BORIC ACID

Ultracruz Antibacteria Lotion

Active Ingredient:

Benzalkonium Chloride 0.1%

Purpose:

Antiseptic

Uses:

Kill germs while soothing skin. Contains Vintamin E and Aloe Vera

Directions:

Aquirt as needed into your palms and thoroughly spread on both hands

Warnings

For external use only

Flammable. Keep away from fire or flame

Do not apply around eyes. Do not use in ears & mouth

When using this product, avoid contatc with eyes. In case of contact, flush eys with water

Stop use and see a doctor if irritation or redness develop and persist for more than 72 hours

Keep out of reach of children. Children must be supervised in use of this product.

Other Information:

Store at 20C (68-77F). May discolor fabrics

Inactive Ingredient:

Deionized water, Vitamin E, Aloe vera, Glycerol, Boric acid, Carbomer, TX-20, Triethanolamine, White oil, Fragrance